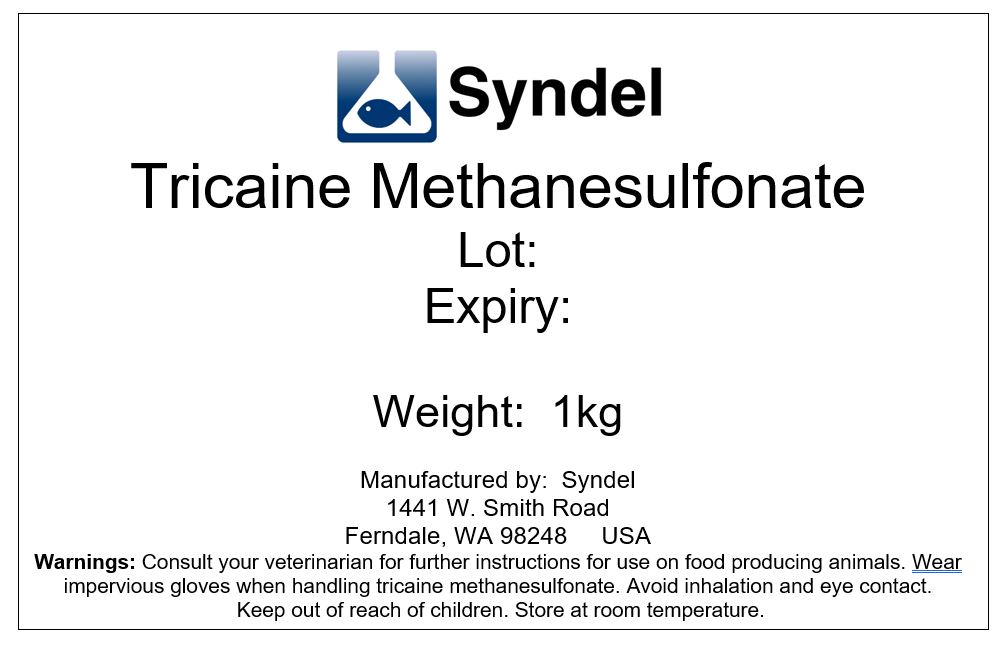 DRUG LABEL: Tricaine methanesulfonate
NDC: 50378-016 | Form: POWDER, FOR SOLUTION
Manufacturer: Western Chemical Inc.
Category: animal | Type: OTC ANIMAL DRUG LABEL
Date: 20230531

ACTIVE INGREDIENTS: TRICAINE METHANESULFONATE 1000 mg/1 g

Tricaine methanesulfonate

WARNINGS AND PRECAUTIONS

Warnings: Consult your veterinarian for furhter instructions for use on food producing animals. Wear impervious gloves when handling tricaine methanesulfonate. Avoid inhalation and eye contact. Kepp out of reach of children. Store at room temperature.

PACKAGE LABEL

Add image transcription here...